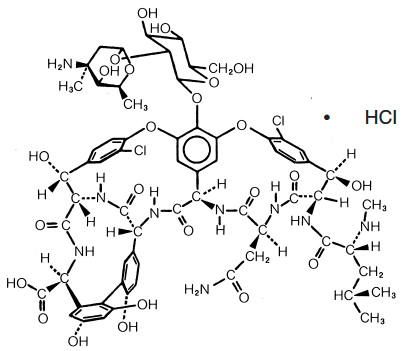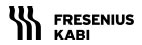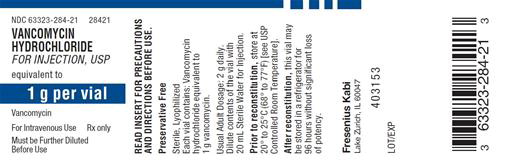 DRUG LABEL: VANCOMYCIN HYDROCHLORIDE
NDC: 63323-284 | Form: INJECTION, POWDER, LYOPHILIZED, FOR SOLUTION
Manufacturer: Fresenius Kabi USA, LLC
Category: prescription | Type: HUMAN PRESCRIPTION DRUG LABEL
Date: 20241015

ACTIVE INGREDIENTS: VANCOMYCIN HYDROCHLORIDE 1 g/20 mL

Vancomycin Hydrochloride for Injection USP

Rx only

To reduce the development of drug-resistant bacteria and maintain the effectiveness of Vancomycin Hydrochloride for Injection, USP and other antibacterial drugs, Vancomycin Hydrochloride for Injection, USP should be used only to treat or prevent infections that are proven or strongly suspected to be caused by bacteria.

DESCRIPTION:

Vancomycin Hydrochloride for Injection, USP is a lyophilized powder, for preparing intravenous (IV) infusions, in vials each containing the equivalent of 1 g vancomycin base. 500 mg of the base are equivalent to 0.34 mmol. When reconstituted with Sterile Water for Injection to a concentration of 50 mg/mL, the pH of the solution is between 2.5 and 4.5. Vancomycin Hydrochloride for Injection, USP should be administered intravenously in diluted solution (see DOSAGE AND ADMINISTRATION). FURTHER DILUTION IS REQUIRED BEFORE USE.

Vancomycin is a tricyclic glycopeptide antibiotic derived from Amycolatopasis orientalis (formerly Nocardia orientalis). Vancomycin hydrochloride has the following structural formula:

C66H75Cl2N9O24• HCl M.W. 1485.73

CLINICAL PHARMACOLOGY:

Vancomycin is poorly absorbed after oral administration.

In subjects with normal kidney function, multiple IV dosing of 1 g of vancomycin (15 mg/kg) infused over 60 minutes produces mean plasma concentrations of approximately 63 mcg/mL immediately at the completion of infusion, mean plasma concentrations of approximately 23 mcg/mL two hours after infusion, and mean plasma concentrations of approximately 8 mcg/mL 11 hours after the end of the infusion. Multiple dosing of 500 mg infused over 30 minutes produces mean plasma concentrations of about 49 mcg/mL at the completion of infusion, mean plasma concentrations of about 19 mcg/mL two hours after infusion, and mean plasma concentrations of about 10 mcg/mL six hours after infusion. The plasma concentrations during multiple dosing are similar to those after a single dose.

The mean elimination half-life of vancomycin from plasma is four to six hours in subjects with normal renal function. In the first 24 hours, about 75% of an administered dose of vancomycin is excreted in urine by glomerular filtration. Mean plasma clearance is about 0.058 L/kg/hr, and mean renal clearance is about 0.048 L/kg/hr. Renal dysfunction slows excretion of vancomycin. In anephric patients, the average half-life of elimination is 7.5 days. The distribution coefficient is from 0.3 to 0.43 L/kg. There is no apparent metabolism of the drug. About 60% of an intraperitoneal dose of vancomycin administered during peritoneal dialysis is absorbed systemically in six hours. Serum concentrations of about 10 mcg/mL are achieved by intraperitoneal injection of 30 mg/kg of vancomycin. Vancomycin is not effectively removed by either hemodialysis or peritoneal dialysis; there have been no reports of vancomycin clearance with hemoperfusion.

Total systemic and renal clearance of vancomycin may be reduced in the elderly.

Vancomycin is approximately 55% serum protein bound as measured by ultrafiltration at vancomycin serum concentrations of 10 to 100 mcg/mL. After IV administration of vancomycin inhibitory concentrations are present in pleural, pericardial, ascitic and synovial fluids; in urine; in peritoneal dialysis fluid; and in atrial appendage tissue. Vancomycin does not readily diffuse across normal meninges into the spinal fluid; but, when the meninges are inflamed, penetration into the spinal fluid occurs.

Microbiology

The bactericidal action of vancomycin results primarily from inhibition of cell-wall biosynthesis. In addition, vancomycin alters bacterial-cell-membrane permeability and RNA synthesis. There is no cross-resistance between vancomycin and other antibiotics. Vancomycin is not active in vitro against gram-negative bacilli, mycobacteria, or fungi.

Synergy

The combination of vancomycin and an aminoglycoside acts synergistically in vitro against many strains of Staphylococcus aureus, Streptococcus bovis, enterococci, and the viridans group streptococci.

Vancomycin has been shown to be active against most strains of the following microorganisms, both in vitro and in clinical infections as described in INDICATIONS AND USAGE.

Aerobic gram-positive microorganisms

Diphtheroids

Enterococci (e.g., Enterococcus faecalis)

Staphylococci, including Staphylococcus aureus and Staphylococcus epidermidis (including heterogeneous methicillin-resistant strains)

Streptococcus bovis

Viridans group streptococci

The following in vitro data are available, but their clinical significance is unknown.

Vancomycin exhibits in vitro MICs of 1 mcg/mL or less against most (≥90%) strains of streptococci listed below and MICs of 4 mcg/mL or less against most (≥90%) strains of other listed microorganisms; however, the safety and effectiveness of vancomycin in treating clinical infections due to these microorganisms have not been established in adequate and well-controlled clinical trials.

Aerobic gram-positive microorganisms

Listeria monocytogenes

Streptococcus pyogenes

Streptococcus pneumoniae (including penicillin-resistant strains)

Streptococcus agalactiae

Anaerobic gram-positive microorganisms

Actinomyces species

Lactobacillus species

Susceptibility Tests

Dilution Techniques

Quantitative methods are used to determine antimicrobial minimum inhibitory concentrations (MICs). These MICs provide estimates of the susceptibility of bacteria to antimicrobial compounds. The MICs should be determined using a standardized procedure. Standardized procedures are based on a dilution method^1 (broth or agar) or equivalent with standardized inoculum concentrations and standardized concentrations of vancomycin powder. The MIC values should be interpreted according to the following criteria:

For testing aerobic microorganismsa other than streptococci:

MIC (mcg/mL) | Interpretation
≤4 | Susceptible (S)
8 to 16 | Intermediate (I)
≥32 | Resistant (R)
a A ß-lactamase test using an inoculum ≥ 10^7 CFU/mL (or direct colony growth) and a nitrocefin-based substrate should be performed to detect either ampicillin or penicillin resistance among enterococci due to ß-lactamase production.

For testing streptococcia other than Streptococcus pneumoniae:

MIC (mcg/mL) | Interpretation
≤1 | Susceptible (S)
a Interpretative criteria applicable only to tests performed by broth microdilution method using cation-adjusted Mueller-Hinton broth with 2 to 5% lysed horse blood^1.

The current absence of data on resistant strains precludes defining any categories other than “Susceptible”.

Strains yielding MIC results suggestive of a “nonsusceptible” category should be submitted to a reference laboratory for further testing.

A report of “Susceptible” indicates that the pathogen is likely to be inhibited if the antimicrobial compound in the blood reaches the concentrations usually achievable. A report of “Intermediate” indicates that the result should be considered equivocal, and, if the microorganism is not fully susceptible to alternative, clinically feasible drugs, the test should be repeated. This category implies possible clinical applicability in body sites where the drug is physiologically concentrated or in situations where high dosage of drug can be used. This category also provides a buffer zone which prevents small uncontrolled technical factors from causing major discrepancies in interpretation. A report of “Resistant” indicates that the pathogen is not likely to be inhibited if the antimicrobial compound in the blood reaches the concentrations usually achievable; other therapy should be selected. Standardized susceptibility test procedures require the use of laboratory control microorganisms to control the technical aspects of the laboratory procedures. Standard vancomycin powder should provide the following MIC values:

Microorganism |  | MIC (mcg/mL)
Enterococcus faecalis | ATCC 29212 | 1 to 4
Staphylococcus aureus | ATCC 29213 | 0.5 to 2
Streptococcus pneumoniaea | ATCC 49619 | 0.12 to 0.5
a Interpretative criteria applicable only to tests performed by broth microdilution method using cation-adjusted Mueller-Hinton broth with 2 to 5% lysed horse blood^1.

Diffusion Techniques

Quantitative methods that require measurement of zone diameters also provide reproducible estimates of the susceptibility of bacteria to antimicrobial compounds. One such standardized procedure^2 requires the use of standardized inoculum concentrations. This procedure uses paper disks impregnated with 30-mcg vancomycin to test the susceptibility of microorganisms to vancomycin.

Reports from the laboratory providing results of the standard single-disk susceptibility test with a 30-mcg vancomycin disk should be interpreted according to the following criteria:

For testing aerobic microorganisms other than enterococci and streptococci:

Zone Diameter (mm) | Interpretation
≥15 | Susceptible (S)
- | Intermediate (I)
- | Resistant (R)

For testing enterococcia,b:

Zone Diameter (mm) | Interpretation
≥17 | Susceptible (S)
15 to 16 | Intermediate (I)
≤14 | Resistant (R)
a A direct nitrocefin-based ß-lactamase test using direct colony growth should be performed to detect either ampicillin or penicillin resistance among enterococci due to ß-lactamase production.
b When testing for enterococci resistance to vancomycin, plates should be held for a full 24 hours and examined using transmitted light. The presence of a haze or any growth within the zone of inhibition indicates resistance. Those enterococci with intermediate zones of inhibition should be tested by a standardized procedure based on a dilution method^1 (broth or agar) or equivalent.

For testing streptococcia other than Streptococcus pneumoniae:

Zone Diameter (mm) | Interpretation
≥17 | Susceptible (S)
a Interpretative criteria applicable only to tests performed by disk diffusion method using Mueller-Hinton agar with 5% defibrinated sheep blood and incubated in 5% CO2^2.

The current absence of data on resistant strains precludes defining any categories other than “Susceptible”. Strains yielding zone diameter results suggestive of a “nonsusceptible” category should be submitted to a reference laboratory for further testing.

Interpretation should be as stated above for results using dilution techniques. Interpretation involves correlation of the diameter obtained in the disk test with the MIC for vancomycin.

As with standardized dilution techniques, diffusion methods require the use of laboratory control microorganisms that are used to control the technical aspects of the laboratory procedures. For the diffusion technique, the 30-mcg vancomycin disk should provide the following zone diameters in these laboratory test quality control strains:

Microorganism |  | Zone Diameter (mm)
Staphylococcus aureus | ATCC 25923 | 17 to 21
Streptococcus pneumoniaea | ATCC 49619 | 20 to 27
a Interpretative criteria applicable only to tests performed by disk diffusion method using Mueller-Hinton agar with 5% defibrinated sheep blood and incubated in 5% CO2^2.

INDICATIONS AND USAGE:

To reduce the development of drug-resistant bacteria and maintain the effectiveness of Vancomycin Hydrochloride for Injection, USP and other antibacterial drugs, vancomycin should be used only to treat or prevent infections that are proven or strongly suspected to be caused by susceptible bacteria. When culture and susceptibility information are available, they should be considered in selecting or modifying antibacterial therapy. In the absence of such data, local epidemiology and susceptibility patterns may contribute to the empiric selection of therapy.

Vancomycin Hydrochloride for Injection, USP is indicated for the treatment of serious or severe infections caused by susceptible strains of methicillin-resistant (β-lactam-resistant) staphylococci. It is indicated for penicillin-allergic patients, for patients who cannot receive or who have failed to respond to other drugs, including the penicillins or cephalosporins, and for infections caused by vancomycin-susceptible organisms that are resistant to other antimicrobial drugs. Vancomycin is indicated for initial therapy when methicillin-resistant staphylococci are suspected, but after susceptibility data are available, therapy should be adjusted accordingly.

Vancomycin is effective in the treatment of staphylococcal endocarditis. Its effectiveness has been documented in other infections due to staphylococci, including septicemia, bone infections, lower respiratory tract infections, and skin and skin-structure infections. When staphylococcal infections are localized and purulent, antibiotics are used as adjuncts to appropriate surgical measures.

Vancomycin has been reported to be effective alone or in combination with an aminoglycoside for endocarditis caused by S. viridans or S. bovis. For endocarditis caused by enterococci (e.g., E. faecalis) , vancomycin has been reported to be effective only in combination with an aminoglycoside.

Vancomycin has been reported to be effective for the treatment of diphtheroid endocarditis. Vancomycin has been used successfully in combination with either rifampin, an aminoglycoside, or both in early-onset prosthetic valve endocarditis caused by S. epidermidis or diphtheroids.

Specimens for bacteriologic cultures should be obtained in order to isolate and identify causative organisms and to determine their susceptibilities to vancomycin.

The parenteral form of vancomycin may be administered orally for treatment of antibiotic-associated pseudomembranous colitis produced by C. difficile and for staphylococcal enterocolitis. Parenteral administration of vancomycin hydrochloride alone is of unproven benefit for these indications. Vancomycin is not effective by the oral route for other types of infection.

CONTRAINDICATIONS:

Vancomycin is contraindicated in patients with known hypersensitivity to this antibiotic.

WARNINGS:

Rapid bolus administration (e.g., over several minutes) may be associated with exaggerated hypotension and, rarely, cardiac arrest.

Vancomycin should be administered in a diluted solution over a period of not less than 60 minutes to avoid rapid-infusion-related reactions. Stopping the infusion usually results in a prompt cessation of these reactions.

Ototoxicity has occurred in patients receiving vancomycin. It may be transient or permanent. It has been reported mostly in patients who have been given excessive doses, who have an underlying hearing loss, or who are receiving concomitant therapy with another ototoxic agent such as an aminoglycoside. Vancomycin should be used with caution in patients with renal insufficiency because the risk of toxicity is appreciably increased by high, prolonged blood concentrations.

Dosage of vancomycin must be adjusted for patients with renal dysfunction (see PRECAUTIONS and DOSAGE AND ADMINISTRATION).

Clostridium difficile associated diarrhea (CDAD) has been reported with use of nearly all antibacterial agents, including vancomycin, and may range in severity from mild diarrhea to fatal colitis. Treatment with antibacterial agents alters the normal flora of the colon leading to overgrowth of C. difficile.

C. difficile produces toxins A and B which contribute to the development of CDAD. Hypertoxin producing strains of C. difficile cause increased morbidity and mortality, as these infections can be refractory to antimicrobial therapy and may require colectomy. CDAD must be considered in all patients who present with diarrhea following antibiotic use. Careful medical history is necessary since CDAD has been reported to occur over two months after the administration of antibacterial agents.

If CDAD is suspected or confirmed, ongoing antibiotic use not directed against C. difficile may need to be discontinued. Appropriate fluid and electrolyte management, protein supplementation, antibiotic treatment of C. difficile, and surgical evaluation should be instituted as clinically indicated.

PRECAUTIONS:

General

Prescribing vancomycin in the absence of a proven or strongly suspected bacterial infection or a prophylactic indication is unlikely to provide benefit to the patient and increases the risk of the development of drug-resistant bacteria.

Clinically significant serum concentrations have been reported in some patients being treated for active C. difficile-induced pseudomembranous colitis after multiple oral doses of vancomycin.

Prolonged use of vancomycin may result in the overgrowth of nonsusceptible organisms. Careful observation of the patient is essential. If superinfection occurs during therapy, appropriate measures should be taken. In rare instances, there have been reports of pseudomembranous colitis due to C. difficile developing in patients who received IV vancomycin.

In order to minimize the risk of nephrotoxicity when treating patients with underlying renal dysfunction or patients receiving concomitant therapy with an aminoglycoside, serial monitoring of renal function should be performed and particular care should be taken in following appropriate dosing schedules (see DOSAGE AND ADMINISTRATION).

Serial tests of auditory function may be helpful in order to minimize the risk of ototoxicity.

Reversible neutropenia has been reported in patients receiving vancomycin (see ADVERSE REACTIONS). Patients who will undergo prolonged therapy with vancomycin or those who are receiving concomitant drugs which may cause neutropenia should have periodic monitoring of the leukocyte count.

Vancomycin is irritating to tissue and must be given by a secure IV route of administration. Pain, tenderness and necrosis occur with intramuscular (IM) injection of vancomycin or with inadvertent extravasation. Thrombophlebitis may occur, the frequency and severity of which can be minimized by administering the drug slowly as a dilute solution (2.5 to 5 g/L) and by rotating the sites of infusion.

There have been reports that the frequency of infusion-related events (including hypotension, flushing, erythema, urticaria and pruritus) increases with the concomitant administration of anesthetic agents. Infusion-related events may be minimized by the administration of vancomycin as a 60-minute infusion prior to anesthetic induction.

The safety and efficacy of vancomycin administration by the intraperitoneal and intrathecal (intralumbar or intraventricular) routes have not been assessed.

Although the safety and efficacy of vancomycin by the intraperitoneal route have not been established, reports reveal that the product has been given by this route during peritoneal dialysis. Administration of vancomycin by the intraperitoneal route during continuous ambulatory peritoneal dialysis has resulted in over 50 reports of chemical peritonitis that developed in some patients within the 12-hour period after administration. To date, all have been self-limited and ranged from cloudy dialysate alone to severe abdominal pain and fever. Most cloudy dialysates were sterile and some contained increased numbers of white blood cells and polymorphonuclear cells. Fluids usually cleared promptly after discontinuation of the vancomycin.

Information for Patients

Diarrhea is a common problem caused by antibiotics which usually ends when the antibiotic is discontinued. Sometimes after starting treatment with antibiotics, patients can develop watery and bloody stools (with or without stomach cramps and fever) even as late as two or more months after having taken the last dose of the antibiotic. If this occurs, patients should contact their physician as soon as possible.

Patients should be counseled that antibacterial drugs including vancomycin should only be used to treat bacterial infections. They do not treat viral infections (e.g., the common cold). When vancomycin is prescribed to treat a bacterial infection, patients should be told that although it is common to feel better early in the course of therapy, the medication should be taken exactly as directed. Skipping doses or not completing the full course of therapy may (1) decrease the effectiveness of the immediate treatment and (2) increase the likelihood that bacteria will develop resistance and will not be treatable by vancomycin or other antibacterial drugs in the future.

Drug Interactions

Concomitant administration of vancomycin and anesthetic agents has been associated with erythema and histamine-like flushing (see Pediatric Use) and anaphylactoid reactions (see ADVERSE REACTIONS).

Concurrent and/or sequential systemic or topical use of other potentially, neurotoxic and/or nephrotoxic drugs, such as amphotericin B, aminoglycosides, bacitracin, polymyxin B, colistin, viomycin, or cisplatin, when indicated requires careful monitoring.

Carcinogenesis, Mutagenesis, Impairment of Fertility

Although no long-term studies in animals have been performed to evaluate carcinogenic potential, no mutagenic potential of vancomycin was found in standard laboratory tests. No definitive fertility studies have been performed.

Pregnancy

Teratogenic Effects: Pregnancy Category C

In a controlled clinical study, vancomycin was administered to pregnant women for serious staphylococcal infections that were complications of their IV drug abuse to evaluate potential ototoxic and nephrotoxic effects on the infant. Vancomycin was found in cord blood. No sensorineural hearing loss or nephrotoxicity attributable to vancomycin was noted. One infant experienced conductive hearing loss that was not attributed to the administration of vancomycin. Because the number of patients treated in this study was limited and vancomycin was administered only in the second and third trimesters, it is not known whether vancomycin causes fetal harm.

Nursing Mothers

Vancomycin is excreted in human milk. Caution should be exercised when vancomycin is administered to a nursing woman. Because of the potential for adverse events, a decision should be made whether to discontinue nursing or discontinue the drug, taking into account the importance of the drug to the mother.

Pediatric Use

In premature neonates and young infants, it may be appropriate to confirm desired vancomycin serum concentrations. Concomitant administration of vancomycin and anesthetic agents has been associated with erythema and histamine-like flushing in pediatric patients (see ADVERSE REACTIONS).

Geriatrics

The natural decrement of glomerular filtration with increasing age may lead to elevated vancomycin serum concentrations if dosage is not adjusted. Vancomycin dosage schedules should be adjusted in elderly patients (see DOSAGE AND ADMINISTRATION).

ADVERSE REACTIONS:

Infusion-Related Events

During or soon after rapid infusion of vancomycin, patients may develop anaphylactoid reactions, including hypotension (see ANIMAL PHARMACOLOGY), wheezing, dyspnea, urticaria, or pruritus. Rapid infusion may also cause flushing of the upper body (“red neck”) or pain and muscle spasm of the chest and back. These reactions usually resolve within 20 minutes but may persist for several hours. Such events are infrequent if vancomycin is given by a slow infusion over 60 minutes. In studies of normal volunteers, infusion-related events did not occur when vancomycin was administered at a rate of 10 mg/min or less.

Nephrotoxicity

Renal failure, principally manifested by increased serum creatinine or BUN concentrations, especially in patients administered large doses of vancomycin, has been reported rarely. Cases of interstitial nephritis have also been reported rarely. Most of these have occurred in patients who were given aminoglycosides concomitantly or who had pre-existing kidney dysfunction. When vancomycin was discontinued, azotemia resolved in most patients.

Gastrointestinal

Onset of pseudomembranous colitis symptoms may occur during or after antibiotic treatment (see WARNINGS).

Ototoxicity

A few dozen cases of hearing loss associated with vancomycin have been reported. Most of these patients had kidney dysfunction or a pre-existing hearing loss or were receiving concomitant treatment with an ototoxic drug. Vertigo, dizziness, and tinnitus have been reported rarely.

Hematopoietic

Reversible neutropenia, usually starting 1 week or more after onset of therapy with vancomycin or after a total dosage of more than 25 g, has been reported for several dozen patients. Neutropenia appears to be promptly reversible when vancomycin is discontinued. Thrombocytopenia has rarely been reported. Although a causal relationship has not been established, reversible agranulocytosis (granulocytes <500/mm^3) has been reported rarely.

Phlebitis

Inflammation at the injection site has been reported.

Miscellaneous

Infrequently, patients have been reported to have had anaphylaxis, drug fever, nausea, chills, eosinophilia, rashes including exfoliative dermatitis, Stevens-Johnson syndrome, toxic epidermal necrolysis and vasculitis in association with administration of vancomycin.

Chemical peritonitis has been reported following intraperitoneal administration of vancomycin (see PRECAUTIONS).

Post Marketing Reports

The following adverse reactions have been identified during post-approval use of vancomycin. Because these reactions are reported voluntarily from a population of uncertain size, it is not possible to reliably estimate their frequency or establish a causal relationship to drug exposure.

Skin and Subcutaneous Tissue Disorders

Drug Rash with Eosinophilia and Systemic Symptoms (DRESS)

OVERDOSAGE:

Supportive care is advised, with maintenance of glomerular filtration. Vancomycin is poorly removed by dialysis. Hemofiltration and hemoperfusion with polysulfone resin have been reported to result in increased vancomycin clearance. The median lethal intravenous dose is 319 mg/kg in rats and 400 mg/kg in mice.

To obtain up-to-date information about the treatment of overdose, a good resource is your certified Regional Poison Control Center. Telephone numbers of certified poison control centers are listed in the Physicians’ Desk Reference (PDR). In managing overdosage, consider the possibility of multiple drug overdoses, interaction among drugs and unusual drug kinetics in your patient.

DOSAGE AND ADMINISTRATION:

Infusion-related events are related to both the concentration and the rate of administration of vancomycin. Concentrations of no more than 5 mg/mL and rates of no more than 10 mg/min are recommended in adults (see also age-specific recommendations). In selected patients in need of fluid restriction, a concentration up to 10 mg/mL may be used; use of such higher concentrations may increase the risk of infusion-related events. Infusion-related events may occur, however, at any rate or concentration.

Patients with Normal Renal Function

Adults

The usual daily dose is 2 g divided either as 500 mg every six hours or 1 g every 12 hours. Each dose should be administered at no more than 10 mg/min, or over a period of at least 60 minutes, whichever is longer. Other patients factors, such as age or obesity, may call for modification of the usual intravenous daily dose.

Children

The usual intravenous dosage of vancomycin is 10 mg/kg per dose given every 6 hours. Each dose should be administered over a period of at least 60 minutes.

Infants and Neonates

In neonates and young infants, the total daily IV dosage may be lower. In both neonates and infants, an initial dose of 15 mg/kg is suggested, followed by 10 mg/kg every 12 hours for neonates in the first week of life and every eight hours thereafter up to the age of one month. Each dose should be administered over 60 minutes. Close monitoring of serum concentrations of vancomycin may be warranted in these patients.

Patients with Impaired Renal Function and Elderly Patients

Dosage adjustment must be made in patients with impaired renal function. In premature infants and the elderly, greater dosage reductions than expected may be necessary because of decreased renal function. Measurement of vancomycin serum concentrations can be helpful in optimizing therapy, especially in seriously ill patients with changing renal function. Vancomycin serum concentrations can be determined by use of microbiologic assay, radioimmunoassay, fluorescence polarization immunoassay, fluorescence immunoassay or high-pressure liquid chromatography.

If creatinine clearance can be measured or estimated accurately, the dosage for most patients with renal impairment can be calculated using the following table. The dosage of vancomycin per day in mg is about 15 times the glomerular filtration rate in mL/min (see following table).

DOSAGE TABLE FOR VANCOMYCIN IN PATIENTS WITH IMPAIRED RENAL FUNCTION

(Adapted from Moellering et al.^3)

Creatinine Clearance Vancomycin Dose

_______mL/min mg/24 hr_____

100 1,545

90 1,390

80 1,235

70 1,080

60 925

50 770

40 620

30 465

20 310

10 155

The initial dose should be no less than 15 mg/kg, even in patients with mild to moderate renal insufficiency.

The table is not valid for functionally anephric patients. For such patients, an initial dose of 15 mg/kg of body weight should be given to achieve prompt therapeutic serum concentrations. The dose required to maintain stable concentrations is 1.9 mg/kg/24 hr. In patients with marked renal impairment, it may be more convenient to give maintenance doses of 250 to 1,000 mg once every several days rather than administering the drug on a daily basis. In anuria, a dose of 1,000 mg every 7 to 10 days has been recommended.

When only serum creatinine is known, the following formula (based on sex, weight and age of the patient) may be used to calculate creatinine clearance. Calculated creatinine clearances (mL/min) are only estimates. The creatinine clearance should be measured promptly.

Men: Weight (kg) x (140 – age in years)

72 x serum creatinine concentration (mg/dL)

Women: 0.85 x above value

The serum creatinine must represent a steady state of renal function or the estimated value for creatinine clearance will not be valid. Such a calculated clearance is an overestimate of actual clearance in patients with conditions: (1) characterized by decreasing renal function, such as shock, severe heart failure or oliguria; (2) in which a normal relationship between muscle mass and total body weight is not present, such as in obese patients or those with liver disease, edema, or ascites; and (3) accompanied by debilitation, malnutrition or inactivity.

The safety and efficacy of vancomycin administration by the intrathecal (intralumbar or intraventricular) route have not been assessed.

Intermittent infusion is the recommended method of administration.

Preparation and Stability

At the time of use, reconstitute vials of vancomycin with Sterile Water for Injection, USP to a concentration of 50 mg of vancomycin/mL. (See following table for volume of diluent.)

Concentration/Vial | Volume of Diluent
1 g | 20 mL

After reconstitution, the vials may be stored in a refrigerator for 96 hours without significant loss of potency.

Reconstituted solutions of vancomycin (1 g/20 mL) must be further diluted in at least 200 mL of a suitable infusion solution. The desired dose diluted in this manner should be administered by intermittent IV infusion over a period of at least 60 minutes.

Compatibility with Other Drugs and IV Fluids

The following diluents are physically and chemically compatible (with 4 g/L vancomycin hydrochloride):

5% Dextrose Injection, USP

5% Dextrose Injection and 0.9% Sodium Chloride Injection, USP

Lactated Ringer’s Injection, USP

5% Dextrose and Lactated Ringer’s Injection

Normosol®-M and 5% Dextrose

0.9% Sodium Chloride Injection, USP

Isolyte® E

Good professional practice suggests that compounded admixtures should be administered as soon after preparation as is feasible.

Vancomycin solution has a low pH and may cause physical instability of other compounds.

Parenteral drug products should be visually inspected for particulate matter and discoloration prior to administration, whenever solution and container permit.

For Oral Administration

Oral vancomycin is used in treating antibiotic-associated pseudomembranous colitis caused by C. difficile and for staphylococcal enterocolitis. Vancomycin is not effective by the oral route for other types of infections. The usual adult total daily dosage is 500 mg to 2 g given in 3 or 4 divided doses for 7 to 10 days. The total daily dose in children is 40 mg/kg of body weight in 3 or 4 divided doses for 7 to 10 days. The total daily dosage should not exceed 2 g. The appropriate dose may be diluted in 1 oz of water and given to the patient to drink. Common flavoring syrups may be added to the solution to improve the taste for oral administration. The diluted solution may be administered via a nasogastric tube.

HOW SUPPLIED:

Product No. | NDC No.
28421 | 63323-284-21 | Vancomycin Hydrochloride for Injection, USP equivalent to 1 g vancomycin in a 20 mL flip-top vial, in packages of 10.

Store at 20° to 25°C (68° to 77°F) [see USP Controlled Room Temperature].

The container closure is not made with natural rubber latex.

ANIMAL PHARMACOLOGY:

In animal studies, hypotension and bradycardia occurred in dogs receiving an intravenous infusion of vancomycin, 25 mg/kg, at a concentration of 25 mg/mL and an infusion rate of 13.3 mL/min.

REFERENCES:

1. National Committee for Clinical Laboratory Standards. Methods for Dilution Antimicrobial Susceptibility Tests for Bacteria that Grow Aerobically — Fourth Edition. Approved Standard NCCLS Document M7-A4, Vol. 17, No. 2, NCCLS, Wayne, PA, January, 1997.
2. National Committee for Clinical Laboratory Standards. Performance Standards for Antimicrobial Disk Susceptibility Tests — Sixth Edition. Approved Standard NCCLS Document M2-A6, Vol. 17, No. 1, NCCLS, Wayne, PA, January, 1997.
3. Moellering, R.C., Krogstad, D.J., and Greenblatt, D.J.: Vancomycin Therapy in Patients with Impaired Renal Function: A Nomogram for Dosage, Ann. Intern. Med., 94:343, 1981.

Lake Zurich, IL 60047
www.fresenius-kabi.us

451476

Issued: October 2015

PACKAGE LABEL

PACKAGE LABEL – PRINCIPAL DISPLAY – Vancomycin Hydrochloride 1 g Vial Label

NDC 63323-284-21

28421

VANCOMYCIN HYDROCHLORIDE FOR INJECTION, USP

equivalent to

1 g per vial

Vancomycin

For Intravenous Use

Rx only

Must be Further Diluted Before Use